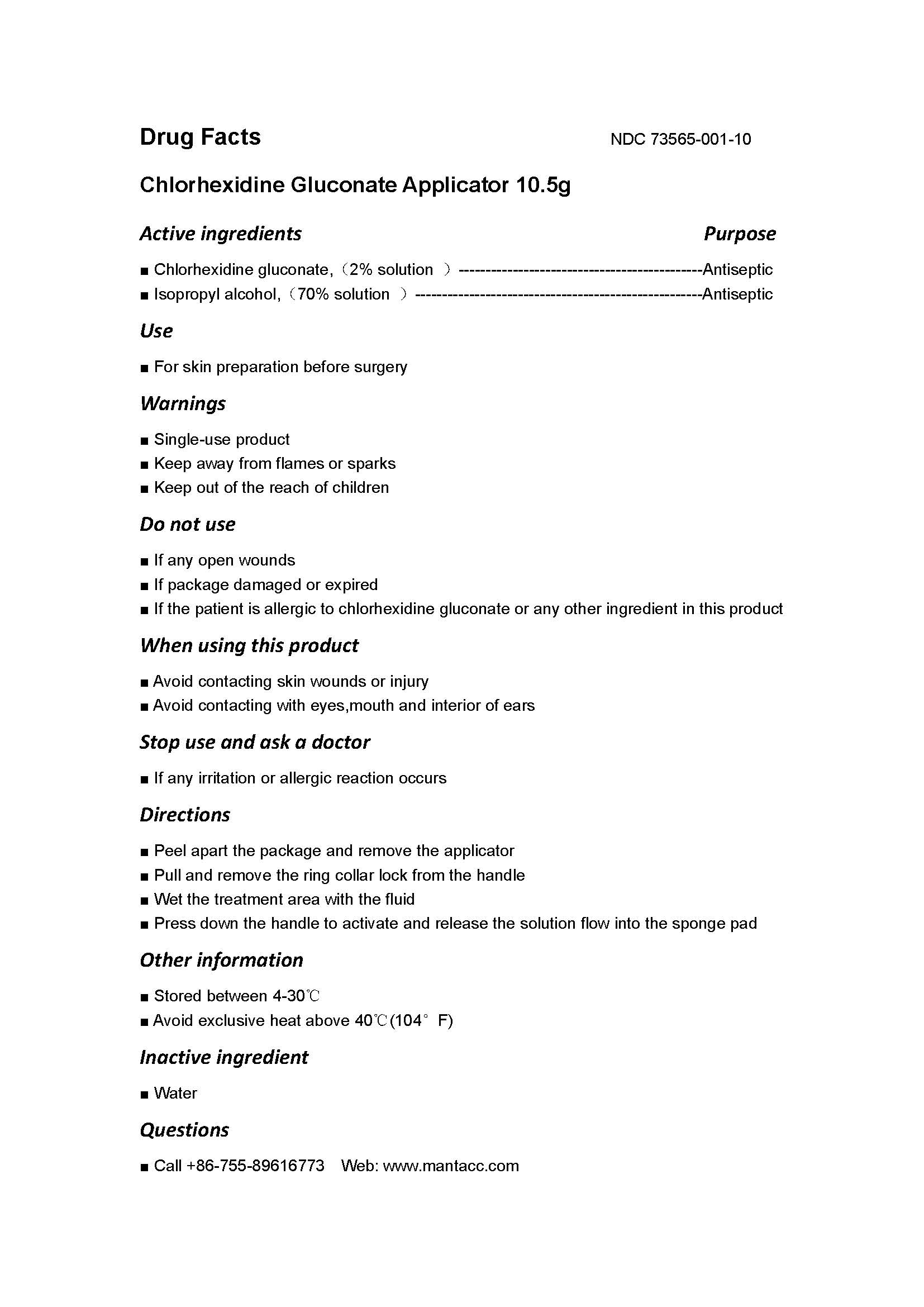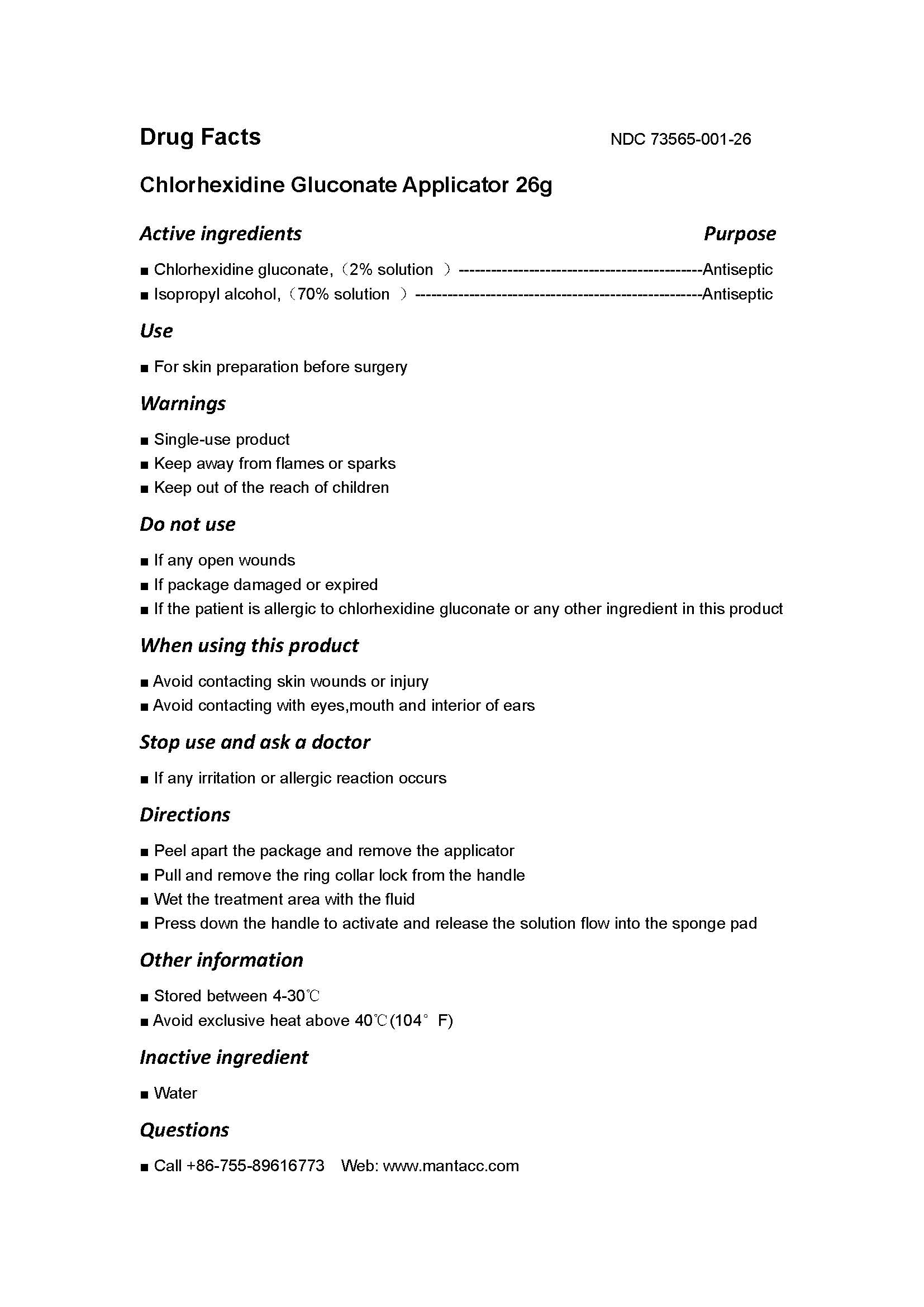 DRUG LABEL: Chlorhexidine Gluconate Applicator
NDC: 73565-011 | Form: SOLUTION
Manufacturer: Miraclean Technology Co.,Ltd
Category: otc | Type: HUMAN OTC DRUG LABEL
Date: 20200224

ACTIVE INGREDIENTS: ISOPROPYL ALCOHOL 70 g/100 g; CHLORHEXIDINE GLUCONATE 2 g/100 g
INACTIVE INGREDIENTS: WATER

Active ingredients

Chlorhexidine gluconate,（ 2% solution ） ，
Isopropyl alcohol,（ 70% solution ）

ask a doctor

If any irritation or allergic reaction occurs

Do not use

■ If any open wounds
■ If package damaged or expired
■ If the patient is allergic to chlorhexidine gluconate or any other ingredient in this product

Keep out of the reach of children

Purpose

Antiseptic

Stop use and ask a doctor

If any irritation or allergic reaction occurs

Inactive ingredient

■ Water

Other information

■ Stored between 4-30℃
Avoid exclusive heat above 40℃ (104° F)

Directions

Peel apart the package and remove the applicator
Pull and remove the ring collar lock from the handle
Wet the treatment area with the fluid
Press down the handle to activate and release the solution flow into the sponge pad

Use

For skin preparation before surgery

Warnings

■ Single-use product
■ Keep away from flames or sparks
■ Keep out of the reach of children